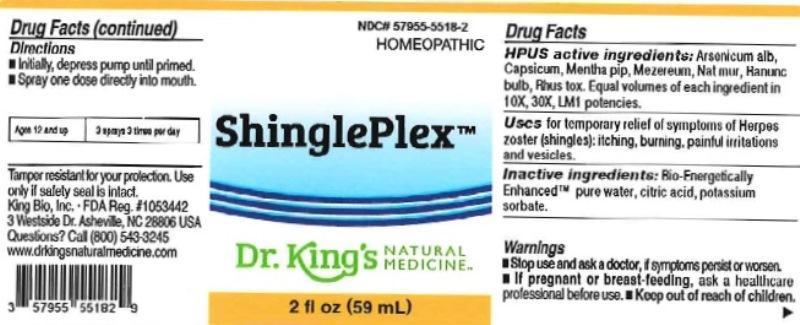 DRUG LABEL: ShinglePlex
NDC: 57955-5518 | Form: LIQUID
Manufacturer: King Bio Inc.
Category: homeopathic | Type: HUMAN OTC DRUG LABEL
Date: 20160318

ACTIVE INGREDIENTS: ARSENIC TRIOXIDE 10 [hp_X]/59 mL; CAPSICUM 10 [hp_X]/59 mL; MENTHA PIPERITA 10 [hp_X]/59 mL; DAPHNE MEZEREUM BARK 10 [hp_X]/59 mL; SODIUM CHLORIDE 10 [hp_X]/59 mL; RANUNCULUS BULBOSUS 10 [hp_X]/59 mL; TOXICODENDRON PUBESCENS LEAF 10 [hp_X]/59 mL
INACTIVE INGREDIENTS: WATER; ANHYDROUS CITRIC ACID; POTASSIUM SORBATE

ShinglePlex™

ACTIVE INGREDIENT

Drug Facts__________________________________________________________________________________________________________

HPUS active ingredients: Arsenicum album, Capsicum annuum, Mentha piperita, Mezereum, Natrum muriaticum, Ranunculus bulbosus, Rhus toxicodendron. Equal volumes of each ingredient in 10X, 30X, and LM1 potencies.

INDICATIONS AND USAGE

Uses for temporary relief of symptoms of Herpes zoster (shingles): itching, burning, painful irritations and vesicles.

Inactive Ingredients:

Bio-Energetically Enhanced™ pure water, citric acid and potassium sorbate.

Warnings

- Stop use and ask your doctor if symptoms persist or worsen.
- If pregnant or breast-feeding, ask a healthcare professional before ues.

- Keep out of reach of children.

Directions

- Initially, depress pump until primed.
- Spray one dose directly into mouth.
- Ages 12 and up: 3 sprays 3 times per day.

OTHER SAFETY INFORMATION

Tamper resistant for your protection. Use only if safety seal is intact.

PURPOSE

Uses for temporary relief of symptoms of Herpes zoster (shingles):

- itching
- burning
- painful irritations
- vesicles.